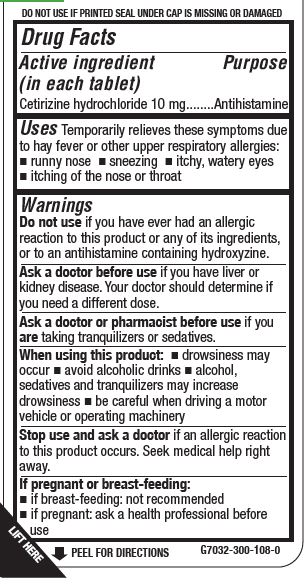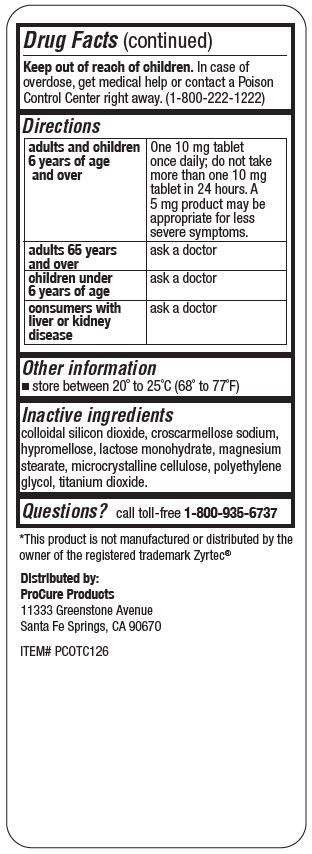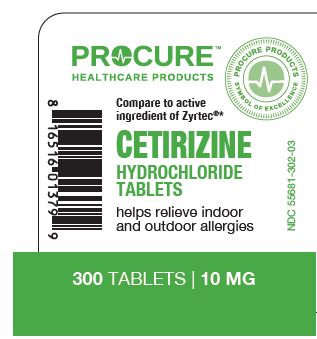 DRUG LABEL: CETIRIZINE HYDROCHLORIDE
NDC: 55681-302 | Form: TABLET
Manufacturer: TWIN MED, LLC
Category: otc | Type: HUMAN OTC DRUG LABEL
Date: 20240103

ACTIVE INGREDIENTS: CETIRIZINE HYDROCHLORIDE 10 mg/1 1
INACTIVE INGREDIENTS: SILICON DIOXIDE; CROSCARMELLOSE SODIUM; HYPROMELLOSE 2208 (100 MPA.S); LACTOSE MONOHYDRATE; MAGNESIUM STEARATE; MICROCRYSTALLINE CELLULOSE; POLYETHYLENE GLYCOL 1000; TITANIUM DIOXIDE

TWIN MED - PROCURE - CETIRIZINE HYDROCHLORIDE TABLETS, 10 MG (55681-302)

Active ingredient (in each tablet)

Cetirizine Hydrochloride 10 mg

PURPOSE

ANTIHISTAMINE

Uses

Temporarily relieves these symptoms due to hay fever or other upper respiratory allergies:

- runny nose
- sneezing
- itchy, watery eyes
- itching of the nose or throat

Warnings

Do not use if you have ever had an allergic reaction to this product or any of its ingredients, or to an antihistamine containing hydroxyzine.

Ask a doctor before use if you have liver or kidney disease. Your doctor should determine if you need a different dose.

Ask a doctor or pharmacist before use if you are taking tranquilizers or sedatives.

When using this product:

- drowsiness may occur
- avoid alcoholic drinks
- alcohol, sedatives and tranquilizers may increase drowsiness
- be careful when driving a motor vehicle or operating machinery

Stop use and ask a doctor if an allergic reaction to this product occurs. Seek medical help right away.

If pregnant or breast-feeding:

- if breast-feeding: not recommended
- if pregnant: ask a health professional before use

Keep out of reach of children. In case of overdose, get medical help or contact a Poison Control Center right away (1-800-222-1222)

Directions

adults and children 6 years of age and over | One 10 mg tablet once daily; do not take more than one 10mg tablet in 24 hours. A 5mg product may be appropriate for less severe symptoms.
adults 65 years and older | ask a doctor
children under 6 years of age | ask a doctor
consumers with liver or kidney disease | ask a doctor

Other information

- store between 20° and 25°C (68° and 77°F)

Inactive ingredients

colloidal silicon dioxide, croscarmellose sodium, hypromellose, lactose monohydrate, magnesium stearate, microcrystalline cellulose, polyethylene glycol, titanium dioxide

Questions?

call toll-free 1-800-935-6737